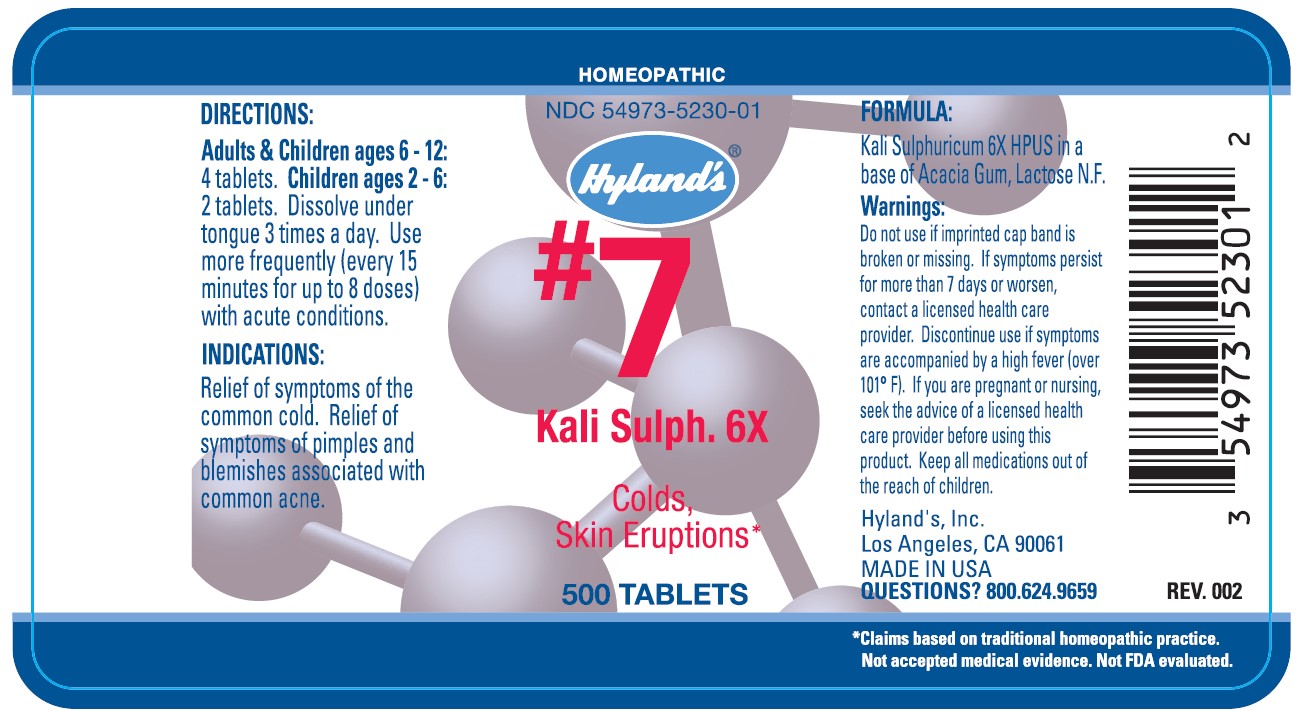 DRUG LABEL: KALI SULPH
NDC: 54973-5230 | Form: TABLET
Manufacturer: Hyland's Inc.
Category: homeopathic | Type: HUMAN OTC DRUG LABEL
Date: 20221219

ACTIVE INGREDIENTS: POTASSIUM SULFATE 6 [hp_X]/1 1
INACTIVE INGREDIENTS: ACACIA; LACTOSE

#7 KALI SULPH. 6X 500 Tablets

DIRECTIONS

Adults & Children ages 6 - 12: 4 tablets. Children ages 2 - 6: 2 tablets. Dissolve under tongue 3 times a day. Use more frequently (every 15 minutes for up to 8 doses) with acute conditions.

INDICATIONS

PURPOSE

Relief of symptoms of the common cold. Relief of symptoms of pimples and blemishes associated with common acne.

FORMULA

Kali Sulphuricum 6X HPUS

INACTIVE INGREDIENT

In a base of Acacia Gum, Lactose N.F.

Warnings

Do not use if imprinted cap band is broken or missing.

ASK DOCTOR

If symptoms persist for more than seven days or worsen, contact a licensed health care provider.

STOP USE

Discontinue use if symptoms are accompanied by a high fever (over 101° F).

PREGNANCY OR BREAST FEEDING

If you are pregnant or nursing, seek the advice of a licensed health care provider before using this product.

KEEP OUT OF REACH OF CHILDREN

Keep this and all medications out of the reach of children.

QUESTIONS?

800.624.9659

PRINCIPAL DISPLAY PANEL - 500 Tablet Bottle Label

HOMEOPATHIC

NDC 54973-5230-01

Hyland's®

#7
Kali Sulph. 6X

Colds,
Skin Eruptions

500 TABLETS